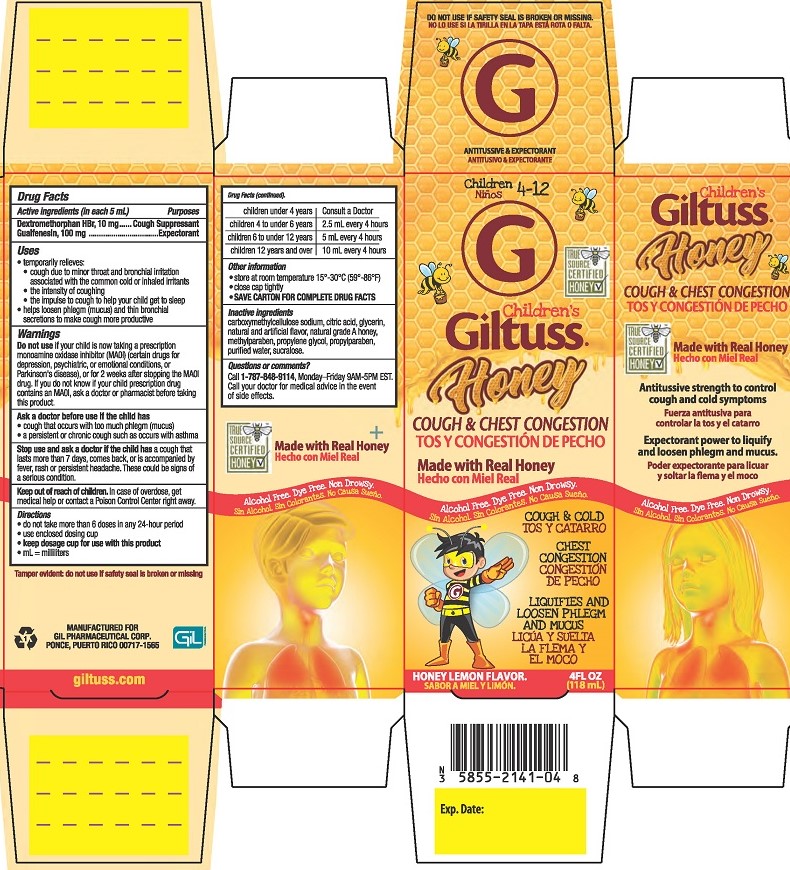 DRUG LABEL: Childrens Giltuss Honey Cough and Chest Congestion
NDC: 58552-141 | Form: SOLUTION
Manufacturer: Gil Pharmaceutical Corp
Category: otc | Type: HUMAN OTC DRUG LABEL
Date: 20251009

ACTIVE INGREDIENTS: GUAIFENESIN 100 mg/5 mL; DEXTROMETHORPHAN HYDROBROMIDE 10 mg/5 mL
INACTIVE INGREDIENTS: CARBOXYMETHYLCELLULOSE SODIUM; WATER; GLYCERIN; PROPYLENE GLYCOL; SUCRALOSE; ANHYDROUS CITRIC ACID; HONEY; METHYLPARABEN; PROPYLPARABEN

Childrens Giltuss Honey Cough & Chest Congestion

Drug Facts

Active ingredients (in each 5 mL)

Dextromethorphan HBr, 10 mg

Guaifenesin, 100 mg

Purposes

Cough Suppressant

Expectorant

Uses

- temporarily relieves:
- cough due to minor throat and bronchial irritation associated with the common cold or inhaled irritants
- the intensity of coughing
- the impulse to cough to help your child get to sleep
- helps loosen phlegm (mucus) and thin bronchial secretions to make coughs more productive and drain bronchial tubes

Warnings

DO NOT USE

Do not useif your child is now taking a prescription monoamine oxidase inhibitor (MAOI) (certain drugs for depression, psychiatric, or emotional conditions, or Parkinson’s disease), or for 2 weeks after stopping the MAOI drug. If you do not know if your child's prescription drug contains an MAOI, ask a doctor or pharmacist before taking this product.

Ask a doctor before use if the child has

- cough that occurs with too much phlegm (mucus)
- a persistent or chronic cough as occurs with asthma

Stop use and ask a doctor if the child hasa cough lasts for more than 7 days, comes back, or is accompanied by fever, rash or persistent headache. These could be signs of a serious condition.

Keep out of reach of children.In case of overdose, get medical help or contact a Poison Control Center right away.

Directions

- do not take more than 6 doses in any 24-hour period
- use enclosed dosinc cup
- keep dosage cup for use with this product
- ml = milliliters
  children under 4 years | Consult a doctor
  children 4 to under 6 years | 2.5 mL every 4 hours
  children 6 to under 12 years | 5 mL every 4 hours
  children 12 years and over | 10 mL every 4 hours

Other information

- store at room temperature 15°-30°C (59°-86°F)
- close cap tightly
- SAVE CARTON FOR COMPLETE DRUG FACTS

INACTIVE INGREDIENT

Inactive ingredientscarboxymethycellulose sodium, citric acid, glycerin, natural and artificial flavor, natural grade A honey, methylparaben, propylene glycol, propylparaben, purified water, sucralose.

Questions or comments?Call 1-787-848-9114, Monday-Friday 9AM - 5PM EST. Call your doctor for medical advice in the event of side effects.

Tamper Evident: do not use if safety seal is broken or missing.

MANUFACTURED FOR

GIL PHARMACEUTICAL CORP.

PONCE, PUERTO RICO 00717-1565

giltuss.com

PACKAGE LABEL

Children 4-12

Children's Giltuss®

Honey Cough & Chest Congestion

Made with real honey

Alcohol Free, Dye Free, Non Drowsy

COUGH AND COLD

CHEST CONGESTION

LIQUIFIES AND LOOSENS PHLEGM AND MUCUS

HONEY LEMON FLAVOR

4FL OZ (118 mL)